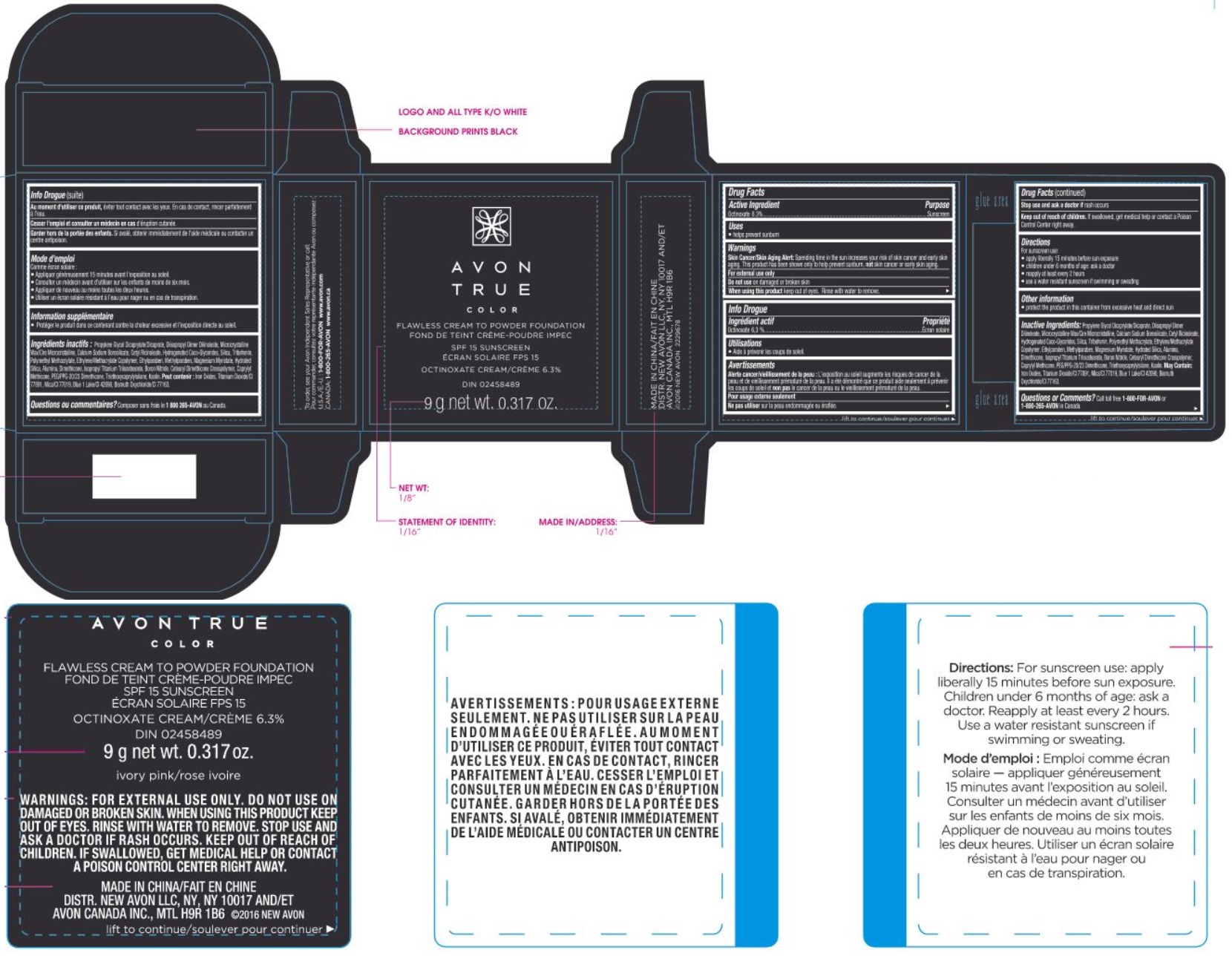 DRUG LABEL: True Color Flawless Cream To Powder Foundation SPF15
NDC: 10096-9505 | Form: CREAM
Manufacturer: New Avon LLC
Category: otc | Type: HUMAN OTC DRUG LABEL
Date: 20180408

ACTIVE INGREDIENTS: OCTINOXATE 6.3 g/100 g
INACTIVE INGREDIENTS: WATER

True Color Flawless Cream To Powder Foundation SPF15

ACTIVE INGREDIENT

Active Ingredients/Ingrédients actifs:

OCTINOXATE (6.3 %)

INDICATIONS & USAGE

Uses

- helps prevent sunburn

WARNINGS

Skin Cancer/Skin Aging Alert: Spending time in the sun increases your risk of skin cancer and early skin aging. This product has been shown only to help prevent sunburn, not skin cancer or early skin aging.

For external use only

Do not use on damaged or broken skin

When using this product keep out of eyes. Rinse with water to remove.

Stop use and ask a doctor if rash occurs

Keep out of reach of children. If swallowed, get medical help or contact a Poison Control Center right away.

DOSAGE & ADMINISTRATION

Directions

- For sunscreen use:
- apply generously and evenly 15 minutes before sun exposure
- children under 6 months of age: ask a doctor
- reapply at least every 2 hours
- use a water resistant sunscreen if swimming or sweating

Other Information

- protect the product in this container from excessive heat and direct sun

INACTIVE INGREDIENT

Inactive Ingredients/Ingrédients inactifs: Propylene Glycol Dicaprylate/Dicaprate, Diisopropyl Dimer Dilinoleate, Microcrystalline Wax/Cire Microcristalline, Calcium Sodium Borosilicate, Cetyl Ricinoleate, Hydrogenated Coco-Glycerides, Silica, Tribehenin, Polymethyl Methacrylate, Ethylene/Methacrylate Copolymer, Ethylparaben, Methylparaben, Magnesium Myristate, Hydrated Silica, Alumina, Dimethicone, Isopropyl Titanium Triisostearate, Boron Nitride, Cetearyl Dimethicone Crosspolymer, Caprylyl Methicone, PEG/PPG-20/23 Dimethicone, Triethoxycaprylylsilane, Kaolin. May Contain: Iron Oxides, Titanium Dioxide/CI 77891, Mica/CI 77019, Blue 1 Lake/CI 42090, Bismuth Oxychloride/CI 77163.

QUESTIONS

Questions or Comments?
Call toll free 1-800-FOR-AVON or 1-800-265-AVON in Canada